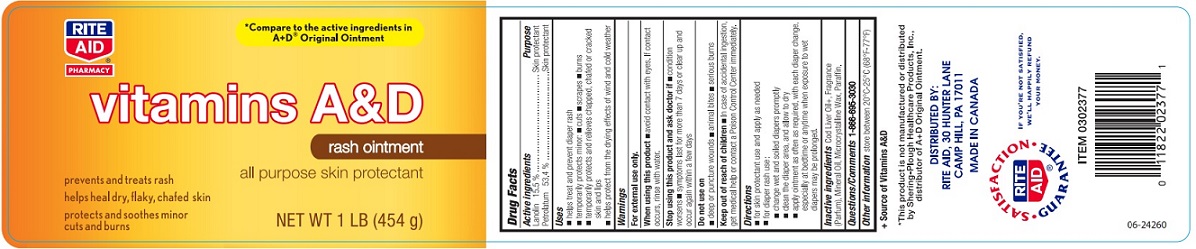 DRUG LABEL: Vitamins A and D Rash
NDC: 11822-3402 | Form: OINTMENT
Manufacturer: Rite Aid
Category: otc | Type: HUMAN OTC DRUG LABEL
Date: 20190814

ACTIVE INGREDIENTS: LANOLIN 15.5 g/100 g; PETROLATUM 53.4 g/100 g
INACTIVE INGREDIENTS: COD LIVER OIL; MINERAL OIL; MICROCRYSTALLINE WAX; PARAFFIN

Drug Facts

Active ingredients

Lanolin 15.5%

Petrolatum 53.4%

Purpose

Skin protectant

Uses

- helps treat and prevent diaper rash
- temporarily protects minor: cuts, scrapes, burns
- temporarily protects and relieves chapped, chafed or cracked skin and lips
- helps protect from the drying effects of wind and cold weather

Warnings

For external use only

When using this product

- avoid contact with eyes. If contact occurs, rinse with water.

Stop using this product and ask doctor if

- condition worsens
- symptoms last for more than 7 days or clear up and occur again within a few days.

Do not use on

- deep or puncture wounds
- animal bites
- serious burns

Keep out of reach of children.

- In case of accidental ingestions, get medical help or contact a Poison Control Center immediately.

Directions

- for skin protectant use and apply as needed
- for diaper rash use: change wet and soiled diapers promptly. Clean the diaper area, and allow to dry. Apply ointment as often as required, with each diaper change, especially at bedtime or anytime when exposure to wet diapers may be prolonged.

Inactive ingredients

Cod Liver Oil, Fragrance (Parfum), Mineral Oil, Microcrystalline Wax, Paraffin.

Questions/Comments

1-866-695-3030

Other information

store between 20°C - 25°C (68°F - 77°F)